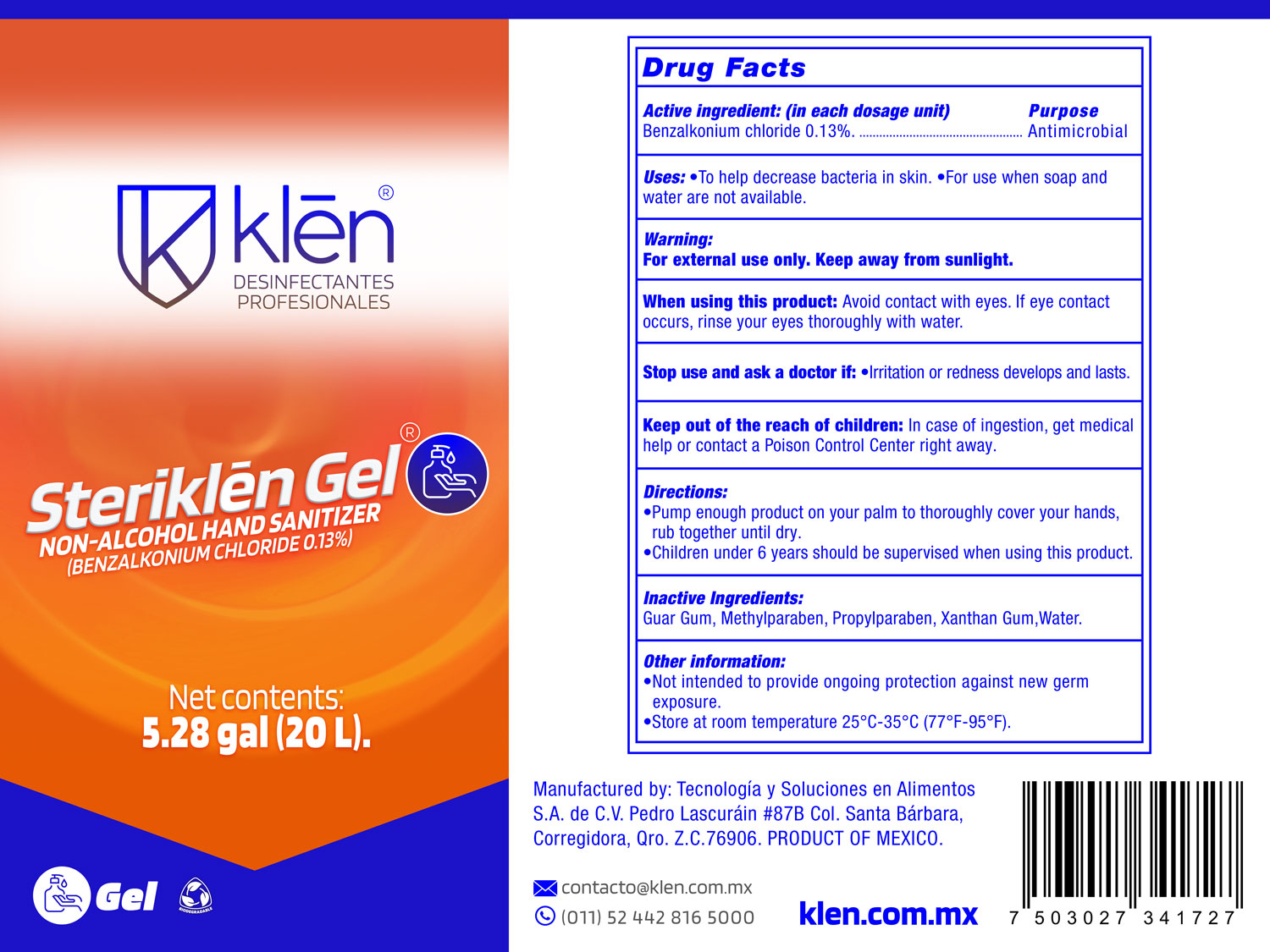 DRUG LABEL: Tecnologia y Soluciones en Alimentos S.A de C.V
NDC: 76945-278 | Form: GEL
Manufacturer: Tecnologia y Soluciones en Alimentos S.A de C.V
Category: otc | Type: HUMAN OTC DRUG LABEL
Date: 20220113

ACTIVE INGREDIENTS: BENZALKONIUM CHLORIDE 13 mg/100 L
INACTIVE INGREDIENTS: GUAR GUM 590 mg/100 L; METHYLPARABEN SODIUM 60 mg/100 L; PROPYLPARABEN SODIUM 30 mg/100 L; WATER 190 mg/100 L

Non Alcohol Hand Sanitizer